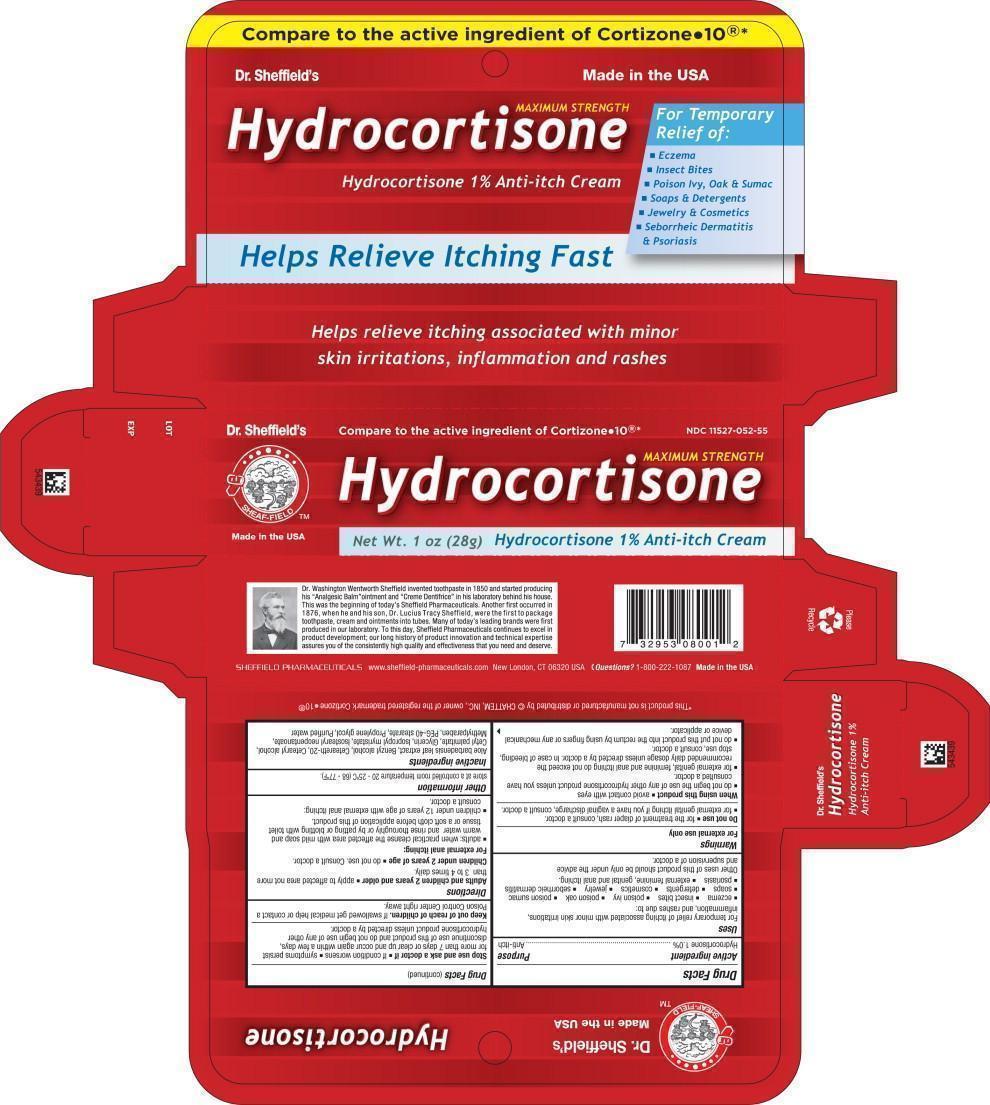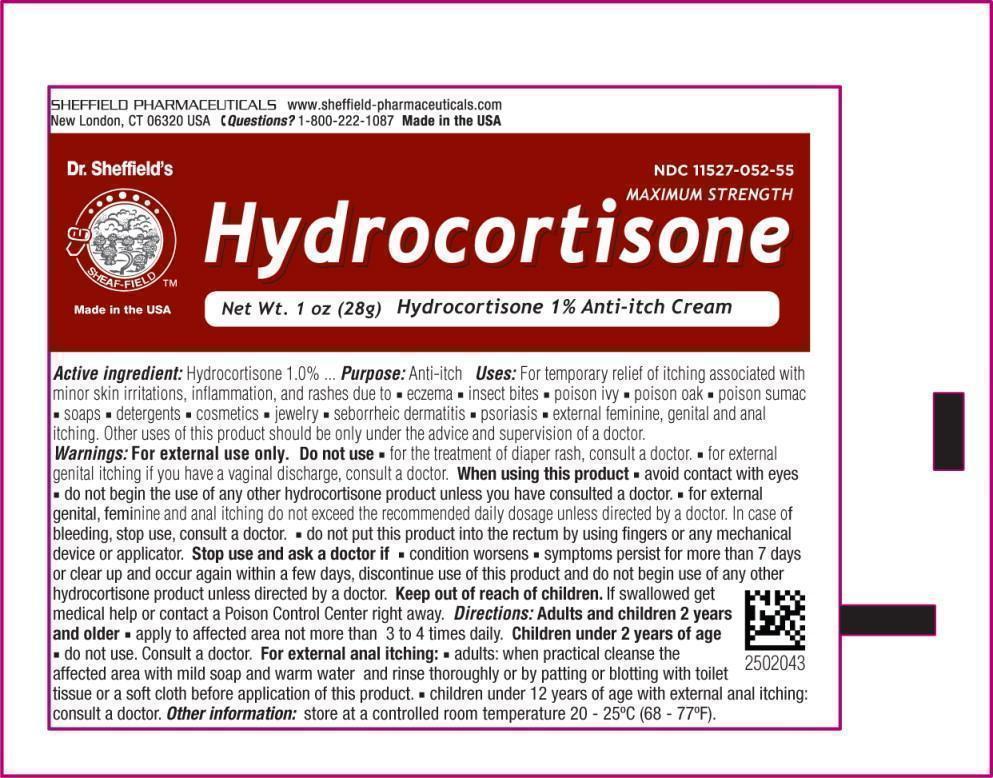 DRUG LABEL: Dr. Sheffield Hydrocortisone Anti itch
NDC: 11527-052 | Form: CREAM
Manufacturer: Sheffield Pharmaceuticals LLC
Category: otc | Type: HUMAN OTC DRUG LABEL
Date: 20231030

ACTIVE INGREDIENTS: Hydrocortisone 10 mg/1 g
INACTIVE INGREDIENTS: ALOE VERA LEAF; BENZYL ALCOHOL; POLYOXYL 20 CETOSTEARYL ETHER; CETOSTEARYL ALCOHOL; CETYL PALMITATE; GLYCERIN; ISOPROPYL MYRISTATE; ISOSTEARYL NEOPENTANOATE; METHYLPARABEN; PEG-40 STEARATE; PROPYLENE GLYCOL; WATER

Drug Facts

Active ingredient

Hydrocortisone 1.0%

Purpose

Anti-itch

Uses

For temporary relief of itching associated with minor skin irritations, inflammation, and rashes due to:

- eczema
- insect bites
- poison ivy
- poison oak
- poison sumac
- soaps
- detergents
- cosmetics
- jewelry
- seborrheic dermatitis
- psoriasis
- external feminine, genital and anal itching.

Other uses of this product should be only under the advice and supervision of a doctor.

Warnings

For external use only

Do not use

- for the treatment of diaper rash, consult a doctor.
- for external genital itching if you have a vaginal discharge, consult a doctor.

When using this product

- avoid contact with eyes
- do not begin the use of any other hydrocortisone product unless you have consulted a doctor.
- for external genital, feminine and anal itching do not exceed the recommended daily dosage unless directed by a doctor. In case of bleeding, stop use, consult a doctor.
- do not put this product into the rectum by using fingers or any mechanical device or applicator.

Stop use and ask a doctor if

- If condition worsens
- symptoms persist for more than 7 days or clear up and occur again within a few days, discontinue use of this product and do not begin use of any other hydrocortisone product unless directed by a doctor.

Keep out of reach of children. If swallowed get medical help or contact a Poison Control Center right away.

Directions

Adults and children 2 years and older

- apply to affected area not more than 3 to 4 times daily.

Children under 2 years of age

- do not use. Consult a doctor.

For external anal itching:

- adults: when practical cleanse the affected area with mild soap and warm water and rinse thoroughly or by patting or blotting with toilet tissue or a soft cloth before application of this product.
- children under 12 years of age with external anal itching: consult a doctor.

Other information

store at a controlled room temperature 20 - 25ºC (68 - 77ºF).

Inactive ingredients

Aloe barbadensis leaf extract, Benzyl alcohol, Ceteareth-20, Cetearyl alcohol, Cetyl palmitate, Glycerin, Isopropyl myristate, Isostearyl neopentanoate, Methylparaben, PEG-40 stearate, Propylene glycol, Purified water

Principal Display Panel – 1oz Carton Label

Compare to the active ingredient of Cortizone●10®*

NDC 11527-052-55

Hydrocortisone MAXIMUM STRENGTH

Net Wt. 1 oz (28g) Hydrocortisone 1% Anti-itch Cream

Dr. Sheffield's

SHEAF-FIELDTM

Made in the USA

Principal Display Panel – 1oz Tube Label

NDC 11527-052-55

Hydrocortisone MAXIMUM STRENGTH

Net Wt. 1 oz (28g) Hydrocortisone 1% Anti-itch Cream

Dr. Sheffield's

SHEAF-FIELDTM

Made in the USA